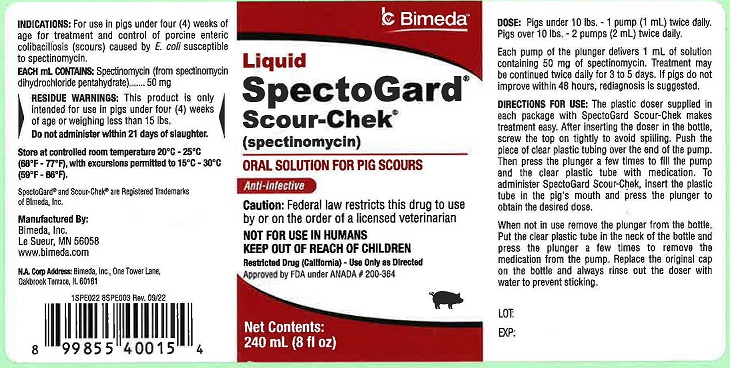 DRUG LABEL: SpectoGard Scour-Chek
NDC: 61133-6002 | Form: SOLUTION
Manufacturer: Bimeda, Inc.
Category: animal | Type: PRESCRIPTION ANIMAL DRUG LABEL
Date: 20241211

ACTIVE INGREDIENTS: Spectinomycin 50 mg/1 mL

DESCRIPTION

Liquid
SpectoGard®
Scour-Chek®
(spectinomycin)
ORAL SOLUTION FOR PIG SCOURS
Anti-infective
Caution: Federal law restricts this drug to use by or on the order of a licensed veterinarian.
NOT FOR USE IN HUMANS
KEEP OUT OF REACH OF CHILDREN
Restricted Drug (California) – Use Only As Directed
Approved by FDA under ANADA # 200-364

INDICATIONS AND USAGE

INDICATIONS: For use in pigs under four (4) weeks of age for treatment and control of porcine enteric colibacillosis (scours) caused by E. coli susceptible to spectinomycin.

EACH mL CONTAINS: Spectinomycin (from spectinomycin dihydrochloride pentahydrate) 50 mg

RESIDUE WARNING

RESIDUE WARNINGS: This product is only intended for use in pigs under four (4) weeks of age or weighing less than 15 lbs.
Do not administer within 21 days of slaughter.

STORAGE AND HANDLING

Store at controlled room temperature 20°C - 25°C (68°F - 77°F), with excursions permitted to 15°C - 30°C (59°F - 86°F).

DOSAGE AND ADMINISTRATION

DOSE: Pigs under 10 lbs. - 1 pump (1 mL) twice daily.
Pigs over 10 lbs. - 2 pumps (2 mL) twice daily.
Each pump of the plunger delivers 1 mL of solution containing 50 mg of spectinomycin. Treatment may be continued twice daily for 3 to 5 days. If pigs do not improve within 48 hours, rediagnosis is suggested.

240 mL:
DIRECTIONS FOR USE: The plastic doser supplied in each package with SpectoGard Scour-Chek makes treatment easy. After inserting the doser in the bottle, screw the top on tightly to avoid spilling. Push the piece of clear plastic tubing over the end of the pump. Then press the plunger a few times to fill the pump and the clear plastic tube with medication. To administer SpectoGard Scour-Chek, insert the plastic tube in the pig's mouth and press the plunger to obtain the desired dose.
When not in use remove the plunger from the bottle. Put the clear plastic tube in the neck of the bottle and press the plunger a few times to remove the medication from the pump. Replace the original cap on the bottle and always rinse out the doser with water to prevent sticking.

1000 mL/1 Gallon:
DIRECTIONS FOR USE: The 1000 mL/1 Gallon bottle of SpectoGard Scour-Chek should be used only to refill the 240 mL bottle in the following manner.
1. Remove the cap and doser from the 240 mL bottle.
2. Unscrew the cap from the 1000 mL/1 Gallon bottle.
3. Pour, from the 1000 mL/1 Gallon bottle, the volume desired.
4. Reinsert the doser in the 240 L bottle and screw the cap on tightly.
5. Screw the cap tightly on the 1000 mL/1 Gallon bottle.